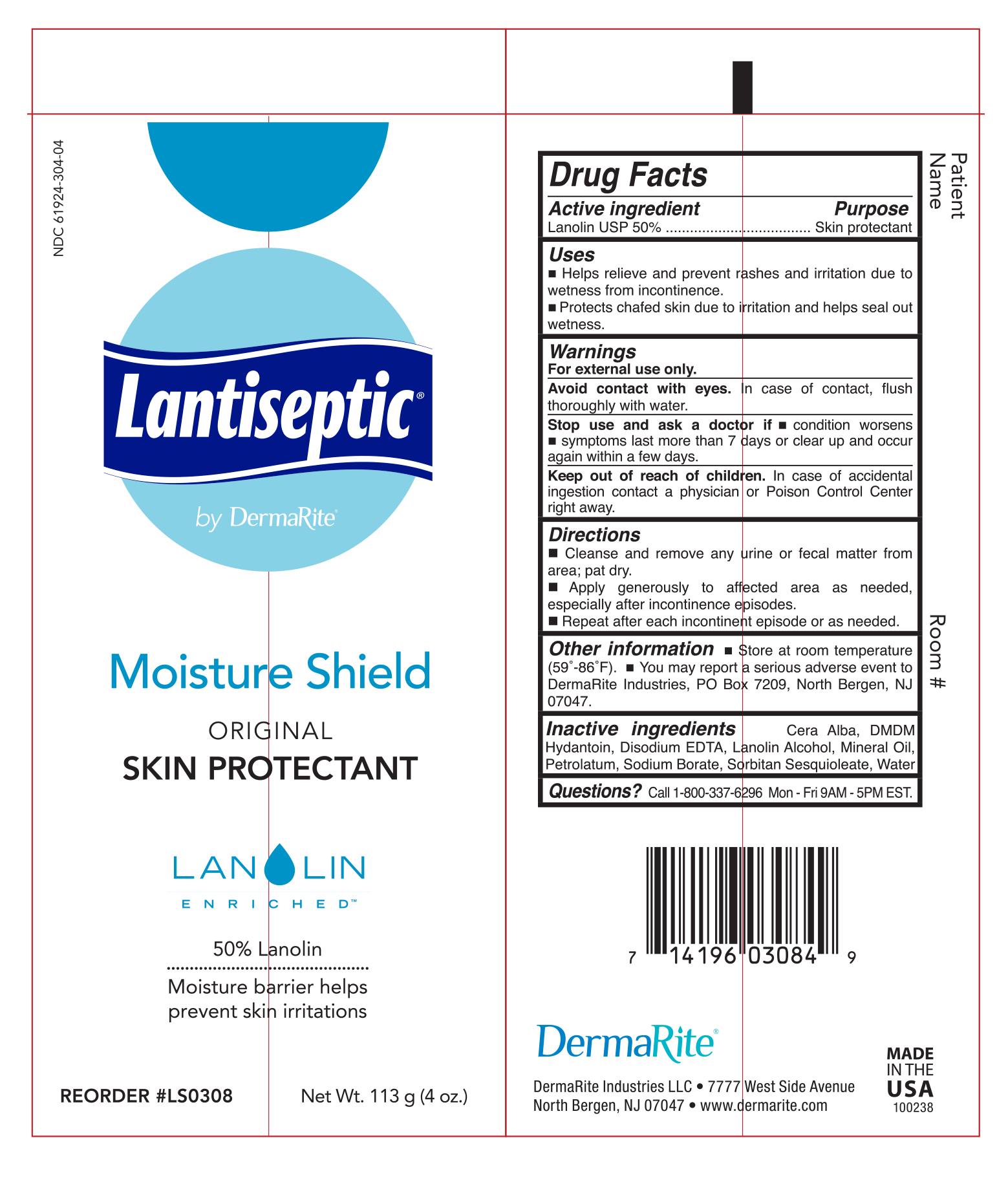 DRUG LABEL: Lantiseptic by DermaRite Original Skin Protectant
NDC: 61924-304 | Form: CREAM
Manufacturer: Dermarite Industries LLC
Category: otc | Type: HUMAN OTC DRUG LABEL
Date: 20241205

ACTIVE INGREDIENTS: LANOLIN 500 mg/1 g
INACTIVE INGREDIENTS: PHENOXYETHANOL; WHITE WAX; EDETATE DISODIUM; LANOLIN ALCOHOLS; MINERAL OIL; PETROLATUM; WATER; SODIUM BORATE; SORBITAN SESQUIOLEATE; CAPRYLYL GLYCOL

Lantiseptic by Dermarite Moisture Shield Original Skin Protectant

Active Ingredient

Lanolin USP 50%

Purpose

Skin Protectant

Uses

- Helps relieve and prevent rashes and irritation due to wetness from incontinence.
- Protects chafed skin due to irritation and helps seal out wetness.

Warnings

For external use only.

Avoid contact with eyes.

In case of contact, flush thoroughly with water.

Stop use and ask a doctor if condition worsens, symptoms last more than 7 days or clear up and occur again within a few days.

Keep out of reach of children. In case of accidental ingestion contact a physician or Poison Control Center right away.

Directions

- Cleanse and remove any urine or fecal matter from area; pat dry.
- Apply generously to affected area as neeeded, especially after incontinence episodes.
- Repeat after each incontinent episode or as needed.

Other Information

- Store at room temperature (59-86°F)
- You may report a serious adverse event to DermaRite Industries, PO box 7209, North Bergen, NJ 07047

Inactive Ingredients

Cera Alba, DMDM Hydantoin, Disodium EDTA, Lanolin Alcohol, Mineral Oil, Petrolatum, Sodium borate, Sorbitan Sesquioleate, Water

Questions or Comments?

Call 1-800-337-6296 Mon-Fri 9AM-5PM EST.